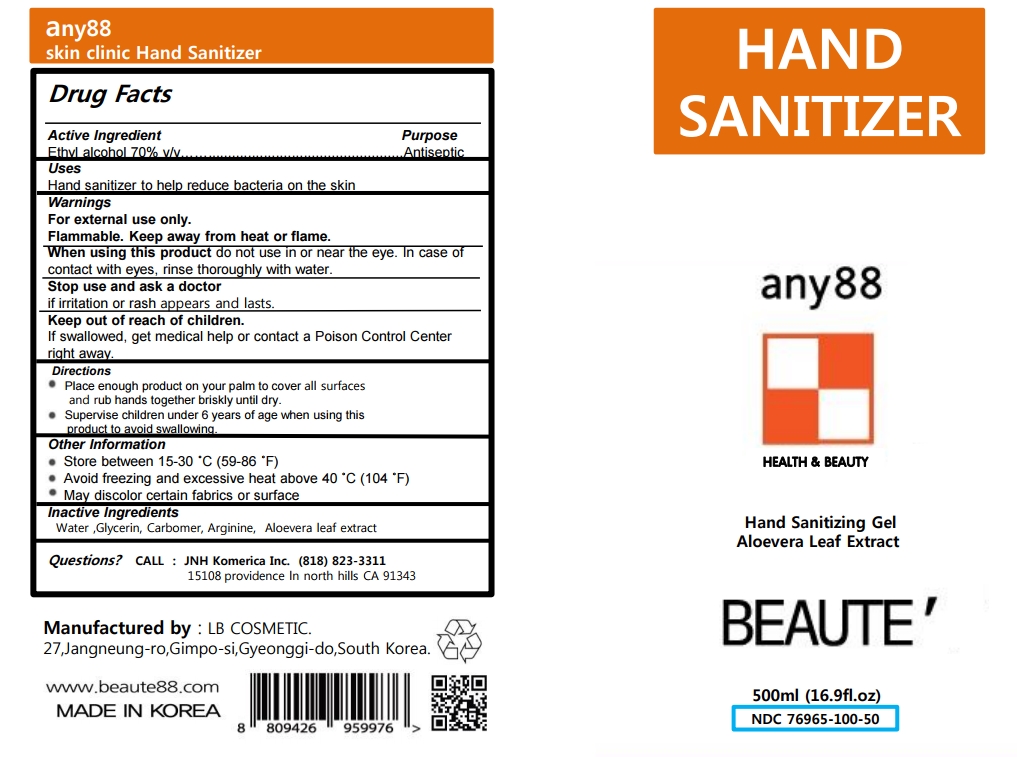 DRUG LABEL: Any88 Skin Clinic Hand Sanitizer
NDC: 76965-100 | Form: GEL
Manufacturer: Beaute cosmetic Co.,Ltd
Category: otc | Type: HUMAN OTC DRUG LABEL
Date: 20200525

ACTIVE INGREDIENTS: ALCOHOL 70 mL/100 mL
INACTIVE INGREDIENTS: CARBOMER HOMOPOLYMER TYPE B (ALLYL PENTAERYTHRITOL CROSSLINKED); ALOE VERA LEAF; GLYCERIN; ARGININE; WATER

Active Ingredient(s)

Alcohol 70% v/v. Purpose: Antiseptic

Purpose

Antiseptic

Use

Hand Sanitizer to help reduce bacteria on the skin

Warnings

For external use only. Flammable. Keep away from heat or flame.

do not use in or near the eye. In case of contact with eyes, rinse thoroughly with water.

Stop use and ask a doctor if irritation or rash appears and lasts.

Keep out of reach of children. If swallowed, get medical help or contact a Poison Control Center right away.

Directions

- Place enough product on your palm to cover all surfaces and rub hands together briskly until dry.
- Supervise children under 6 years of age when using this product to avoid swallowing.

Other information

- Store between 15-30C (59-86F)
- Avoid freezing and excessive heat above 40C (104F)
- May discolor certain fabrics or surface

Inactive ingredients

Water, Glycerin, Carbomer, Arginine, Aloevera Leaf Extract